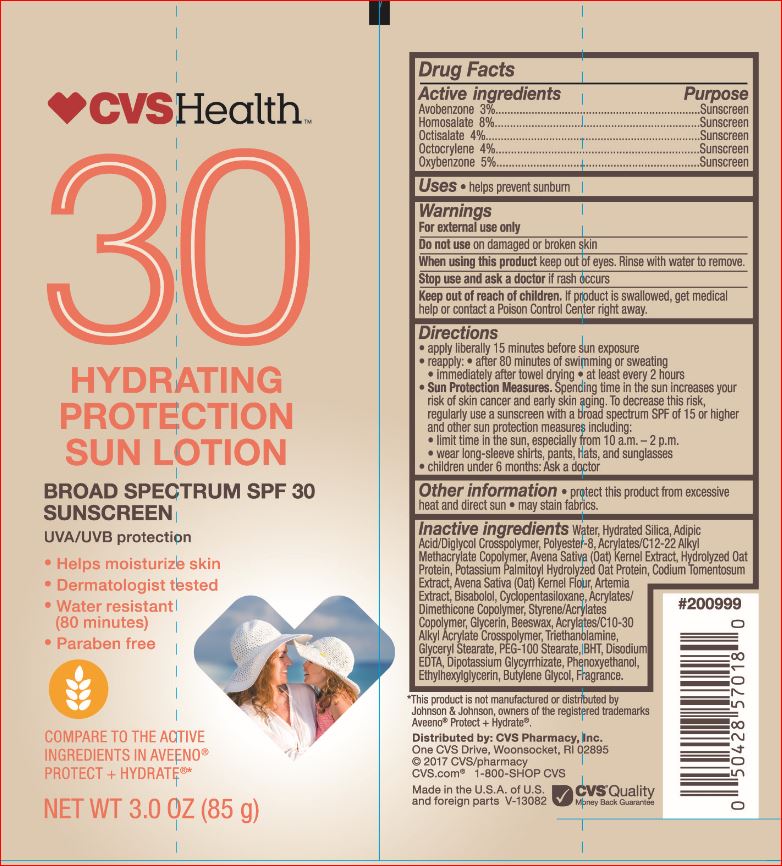 DRUG LABEL: Hydrating Protection Sunscreen SPF 30
NDC: 69842-055 | Form: LOTION
Manufacturer: CVS
Category: otc | Type: HUMAN OTC DRUG LABEL
Date: 20171226

ACTIVE INGREDIENTS: Avobenzone 3 g/100 mL; Homosalate 8 g/100 mL; Octisalate 4 g/100 mL; Octocrylene 4 g/100 mL; Oxybenzone 5 g/100 mL
INACTIVE INGREDIENTS: Water; Hydrated Silica; POLYESTER-8 (1400 MW, CYANODIPHENYLPROPENOYL CAPPED); OAT; CODIUM TOMENTOSUM; LEVOMENOL; CYCLOMETHICONE 5; Glycerin; Yellow wax; TROLAMINE; GLYCERYL MONOSTEARATE; PEG-100 Stearate; BUTYLATED HYDROXYTOLUENE; EDETATE DISODIUM; GLYCYRRHIZINATE DIPOTASSIUM; Phenoxyethanol; Ethylhexylglycerin; Butylene Glycol; ADIPIC ACID/DIGLYCOL CROSSPOLYMER (20000 MPA.S)

Drug Facts

Active ingredients Purpose
Avobenzone 3%..................................................................Sunscreen
Homosalate 8%..................................................................Sunscreen
Octisalate 4%.....................................................................Sunscreen
Octocrylene 4%..................................................................Sunscreen
Oxybenzone 5%.................................................................Sunscreen

INDICATIONS AND USAGE

Uses • helps prevent sunburn

Warnings
For external use only
Do not use on damaged or broken skin
When using this product keep out of eyes. Rinse with water to remove.
Stop use and ask a doctor if rash occurs

Keep out of reach of children. If product is swallowed, get medical help or contact a Poison Control Center right away

Directions
• apply liberally 15 minutes before sun exposure
• reapply: • after 80 minutes of swimming or sweating
• immediately after towel drying • at least every 2 hours
• Sun Protection Measures. Spending time in the sun increases your
risk of skin cancer and early skin aging. To decrease this risk,
regularly use a sunscreen with a broad spectrum SPF of 15 or higher
and other sun protection measures including:
• limit time in the sun, especially from 10 a.m. – 2 p.m.
• wear long-sleeve shirts, pants, hats, and sunglasses
• children under 6 months: Ask a doctor

Inactive ingredients

Water, Hydrated Silica, Adipic
Acid/Diglycol Crosspolymer, Polyester-8, Acrylates/C12-22 Alkyl
Methacrylate Copolymer, Avena Sativa (Oat) Kernel Extract, Hydrolyzed Oat
Protein, Potassium Palmitoyl Hydrolyzed Oat
Protein, Codium Tomentosum Extract, Avena Sativa
(Oat) Kernel Flour, Artemia Extract, Bisabolol,
Cyclopentasiloxane, Acrylates/Dimethicone
Copolymer, Styrene/Acrylates Copolymer, Glycerin,
Beeswax, Acrylates/C10-30 Alkyl Acrylate
Crosspolymer, Triethanolamine, Glyceryl Stearate,
PEG-100 Stearate, BHT, Disodium EDTA,
Dipotassium Glycyrrhizate, Phenoxyethanol,
Ethylhexylglycerin, Butylene Glycol, Fragrance.